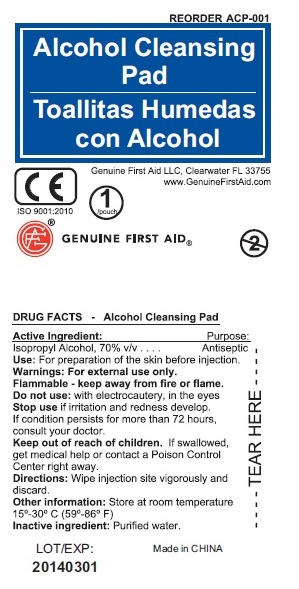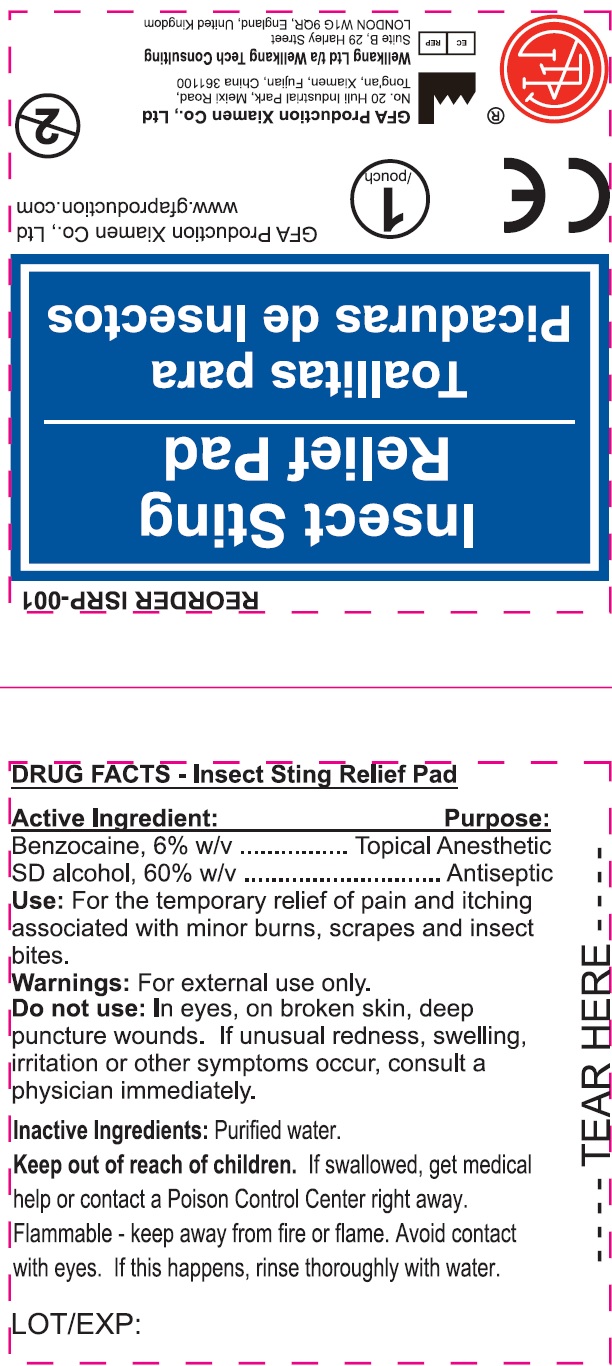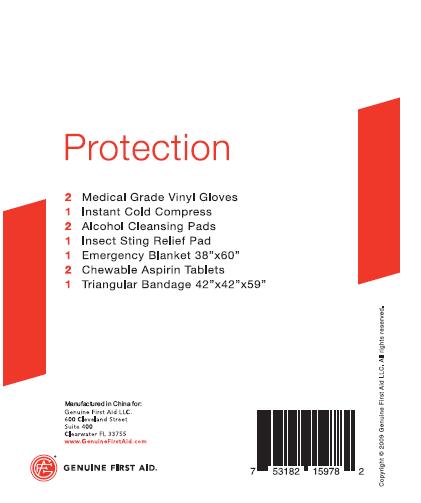 DRUG LABEL: Protection
NDC: 52124-0114 | Form: KIT | Route: TOPICAL
Manufacturer: Genuine First Aid LLC
Category: otc | Type: HUMAN OTC DRUG LABEL
Date: 20210201

ACTIVE INGREDIENTS: ISOPROPYL ALCOHOL 70 mL/100 mL; BENZOCAINE 0.6 mg/100 mL; ALCOHOL 60 mL/100 mL; ASPIRIN 81 mg/1 1
INACTIVE INGREDIENTS: WATER; WATER; FD&C YELLOW NO. 6; SACCHARIN; SODIUM CATION; SILICON DIOXIDE; STARCH, CORN; STEARIC ACID; SUCROSE

Kit5 Protection

Active Ingredient:

Isopropyl Alcohol, 70% v/v

Alcohol Cleansing Pad Use

Use: For preparation of the skin befoire injection.

Warnings: For external use only.

STORAGE AND HANDLING

Flammable - keep away from fire or flame

Do not use: with electrocautery, in the eyes.

Stop use if irritation and redness develop.
If condition persists for more than 72 hours,
consult your doctor.

Keep out of reach of children. If swallowed,
get medical help or contact a Poison Control
Center right away.

WHEN USING

Directions: Wipe injection site vigorously and

Other information: Store at room temperature
15 - 30 degree Celsius (59 - 86 Farenheit)

Inactive Ingredient: Purified water

DESCRIPTION

LOT/EXP: Made in CHINA
20140301

Active Ingredient

Benzocaine, 6% w/v.
SD alcohol, 60% w/v

52124-0008

Use: for the temporary relief of pain and itching associated with minor burn, scrapes, and insect bites.

Warnings: For external use only.
Avoid contact with eyes. If this happens,
rinse thoroughly with water.

Keep out of reach of children. If swallowed, get medical help
or contact a Poison Control Center right away.

STORAGE AND HANDLING

Flammable - keep away from fire or flame.

Do not use: In eyes, on broken skin, deep
puncture wounds. If unusual redness, swelling,
irritation or other symptoms occur, consult a
physician immediately.

DESCRIPTION

Made in CHINA
LOT/EXP:

52124-0008 Inactive Ingredients

Inactive Ingredient: Purified Water

Active Ingredient (in each tablet)

Aspirin 81 mg (NSAID*)

Uses

Temporary relief of minor aches, pains and headaches

to reduce fever associated with colds, sore throats, teething

Warnings

Reye's Syndrome: Children and teenagers who have or are recovering from chicken pox or flu-like symptoms should not use this product. When using this product, if changes in behavior with nausea and vomiting occur, consult a doctor because these symptoms could be an early sign of Reye's syndrome.

Stomach bleeding warning: This product contains a non-steroidal anti-inflammatory drug (NSAID), which may cause stomach bleeding. The chance is higher if the user; has had stomach ulcers or bleeding problems

takes a blood thinning (anticoagulant) or steroid drug
takes other drugs containing prescription or nonprescription NSAIDs (aspirin, ibuprofen, naproxen, or others)
takes more or for a longer time than directed
is age 60 or older

has 3 or more alcoholic drinks every while using this product.

Do not use

if you are allergic to aspirin or any other pain relievers/fever reducers

for more than 10 days for pain unless directed by a doctor

for more than 3 days for fever unless directed by a doctor

for at least 7 days after a tonsillectomy or oral surgery

Ask a doctor before use if you have;

asthma

stomach problems (such as heartburn, upset stomach, or stomach pain) that persist or recur, ulcers or bleeding problems

a child experiencing arthritis pain

if you are;

allergic to aspirin

taking prescription drug for anticoagulation (thinning of blood), diabetes, gout or arthritis

Stop use and ask a doctor if;

an allergic reaction occurs, Seek medical help right away

pain or fever persists

new or unexpected symptoms occur

redness or swelling is present

ringing in ears or loss of hearing occurs

PREGNANCY OR BREAST FEEDING

If pregnant or breast-feeding, ask a health professional before use. It is especially important not to use aspirin during the last 3 months of pregnancy unless definitely directed to do so by a doctor because it may cause problems in unborn child or complications during delivery.

Keep out of reach of children. In case of overdose, get medical help or contact a Poison Control Center immediately.

DOSAGE AND ADMINISTRATION

Directions Do not use more than directed

Adults and Children (12 years and older): Chew 4 to 8 tablets with water every 4 hours, Do not exceed 48 tablets in 24 hours unless directed by a doctor.

Children Under 12 years: Consult a doctor.

STORAGE AND HANDLING

Store at room temperature

tamper evident sealed packets

do not use any opened or torn packets

INACTIVE INGREDIENT

Inactive ingredients flavor, FD and C yellow No. 6, saccharin, sodium, silicon dioxide, starch, stearic acid, sucrose

DESCRIPTION

MADE IN USA

Distributed by GENUINE FIRST AID

600 Cleveland Str Suite 400, Clearwater, FL 33755

Alcohol Cleansing Wipe Purpose

Antiseptic

Insect Sting Relief Pad Purpose

Antiseptic

Aspirin Purpose

Analgesic/Antipyretic